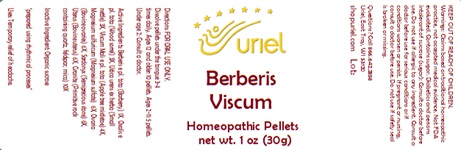 DRUG LABEL: Berberis Viscum
NDC: 48951-2059 | Form: PELLET
Manufacturer: Uriel Pharmacy Inc.
Category: homeopathic | Type: HUMAN OTC DRUG LABEL
Date: 20240112

ACTIVE INGREDIENTS: BERBERIS VULGARIS ROOT BARK 1 [hp_X]/1 1; OXALIS ACETOSELLA LEAF 3 [hp_X]/1 1; URTICA URENS 3 [hp_X]/1 1; VISCUM ALBUM FRUITING TOP 4 [hp_X]/1 1; MAGNESIUM SULFATE, UNSPECIFIED 6 [hp_X]/1 1; BOS TAURUS OVARY 6 [hp_X]/1 1; ALUMINUM OXIDE 6 [hp_X]/1 1; BOS TAURUS UTERUS 6 [hp_X]/1 1; PENOXSULAM 10 [hp_X]/1 1
INACTIVE INGREDIENTS: SUCROSE; LACTOSE, UNSPECIFIED FORM

Berberis Viscum

INDICATIONS AND USAGE

Directions: FOR ORAL USE ONLY.

DOSAGE AND ADMINISTRATION

Dissolve pellets under the tongue 3-4 times daily. Ages 12 and older: 10 pellets. Ages 2-11: 5 pellets. Under age 2: Consult a doctor.

ACTIVE INGREDIENT

Active Ingredients: Berberis e pl. tota 1X, Oxalis e pl. tota 3X, Urtica urens ex herba 3X, Viscum Mali e pl. tota 4X, Magnesium sulfuricum 6X, Ovaria 6X, Sardonyx 6X, Uterus 6X, Granite 10X

Inactive Ingredient: Organic sucrose, Lactose

"prepared using rhythmical processes"

PURPOSE

Uses: Temporary relief of headache.

KEEP OUT OF REACH OF CHILDREN.

WARNINGS

Warnings: Claims based on traditional homeopathic practice, not accepted medical evidence. Not FDA evaluated. Contains sugar. Diabetics and persons intolerant of sucrose (sugar): Consult a doctor before use. Contains lactose. Do not use if allergic to any ingredient. Consult a doctor before use for serious conditions or if conditions worsen or persist. If pregnant or nursing, consult a doctor before use. Do not use if safety seal is broken or missing.

QUESTIONS

Questions? Call 866.642.2858 Uriel, East Troy WI 53120 shopuriel.com